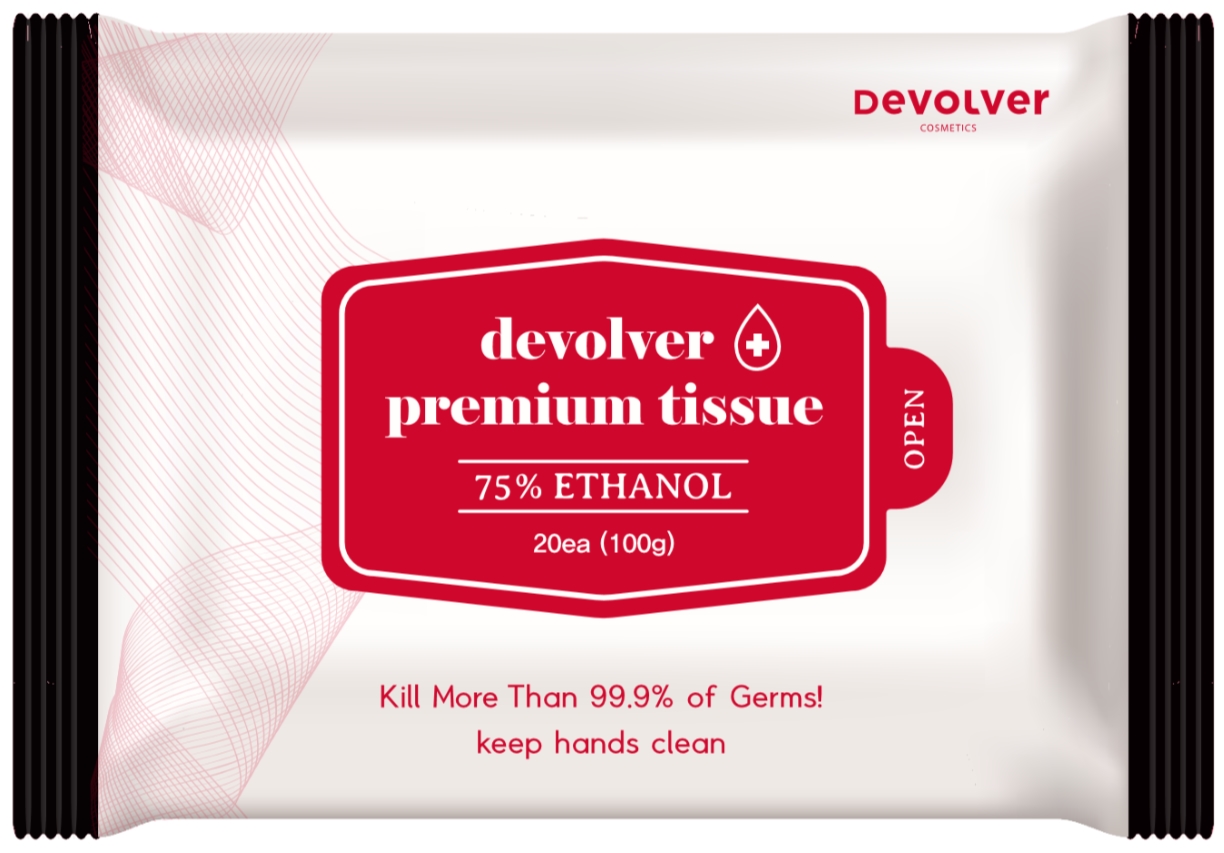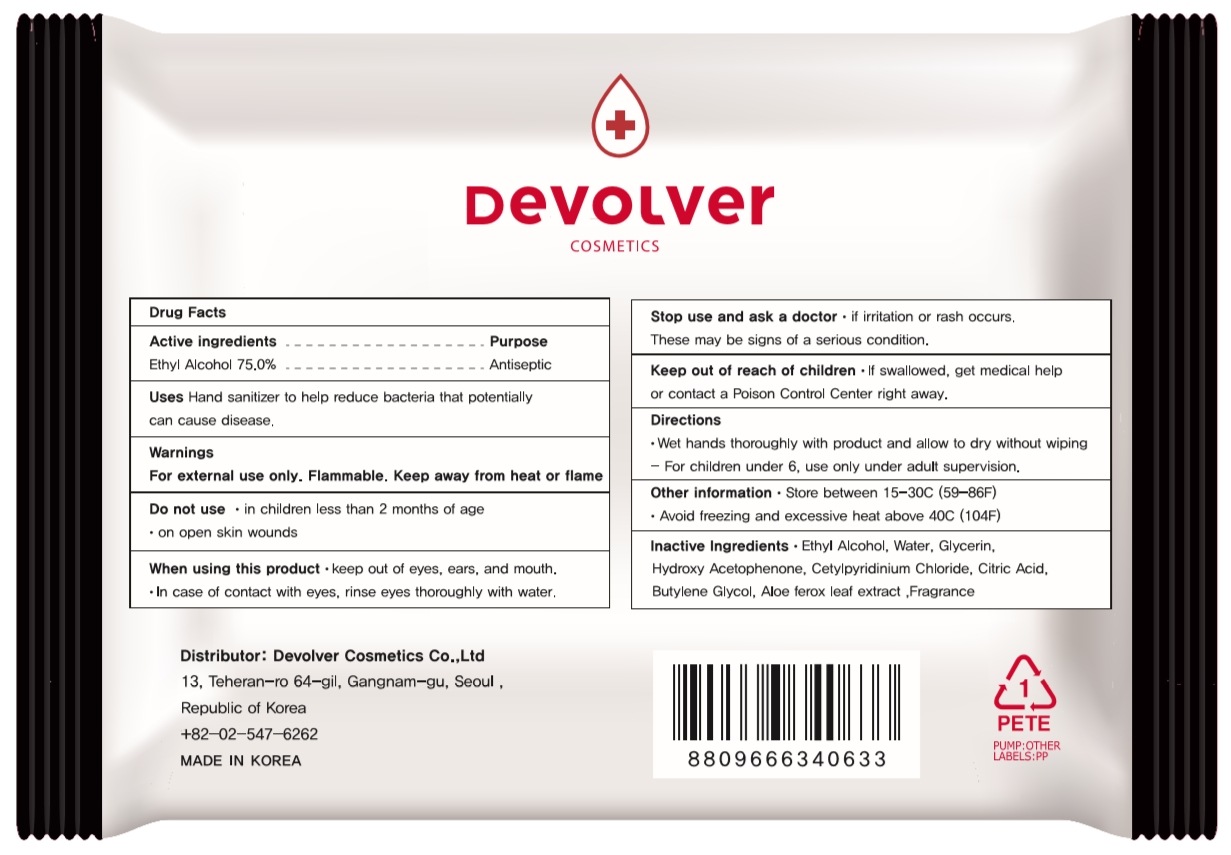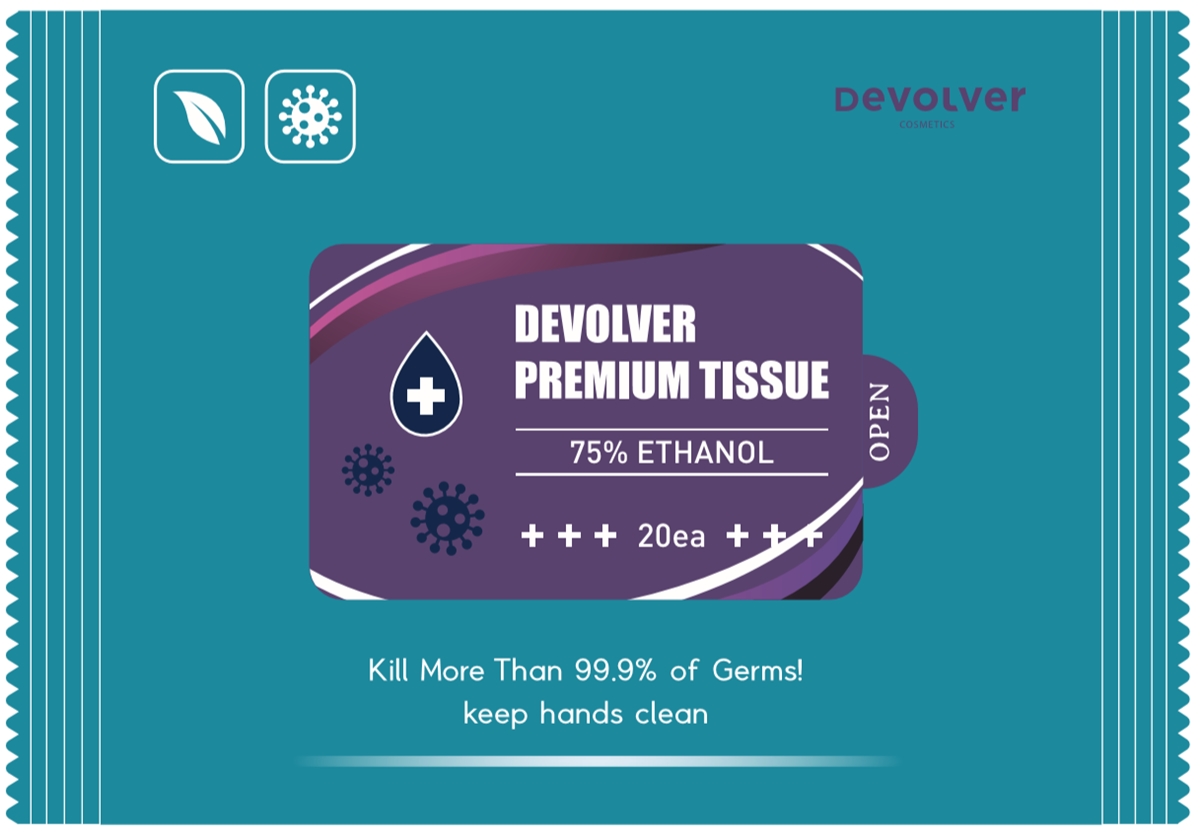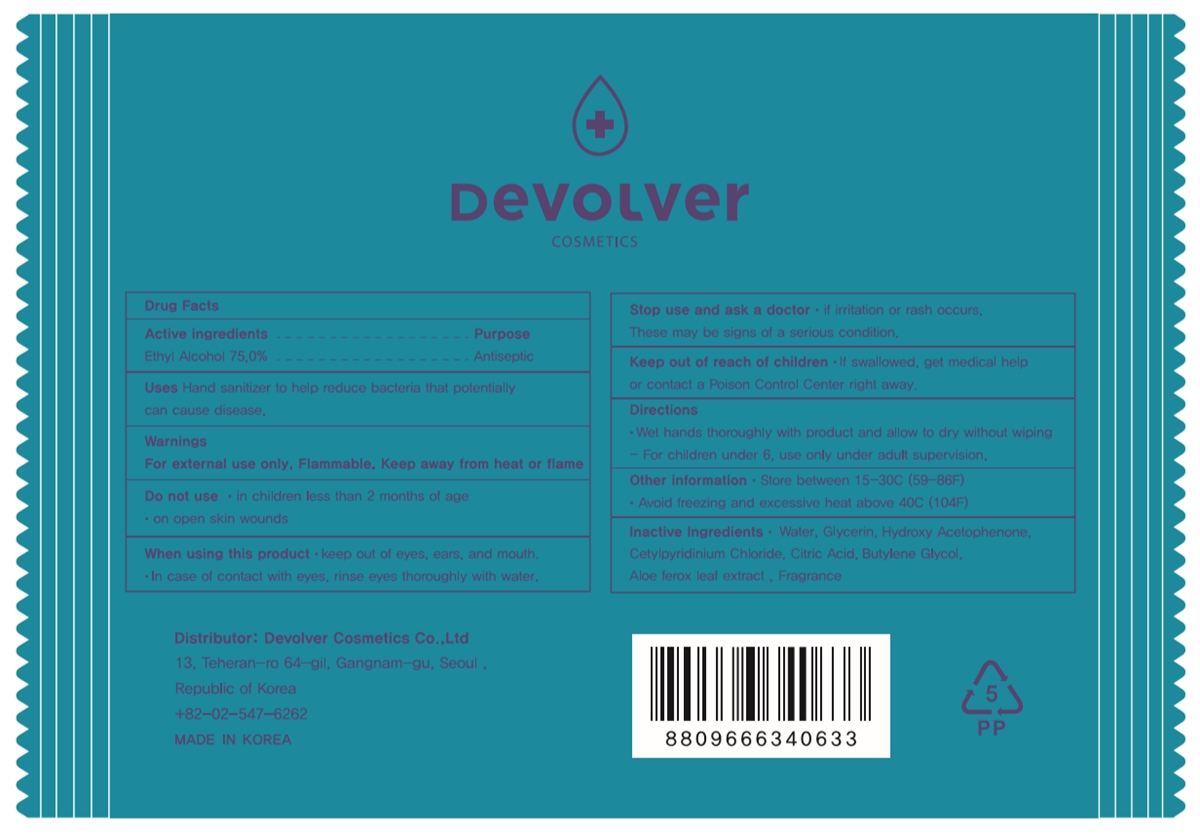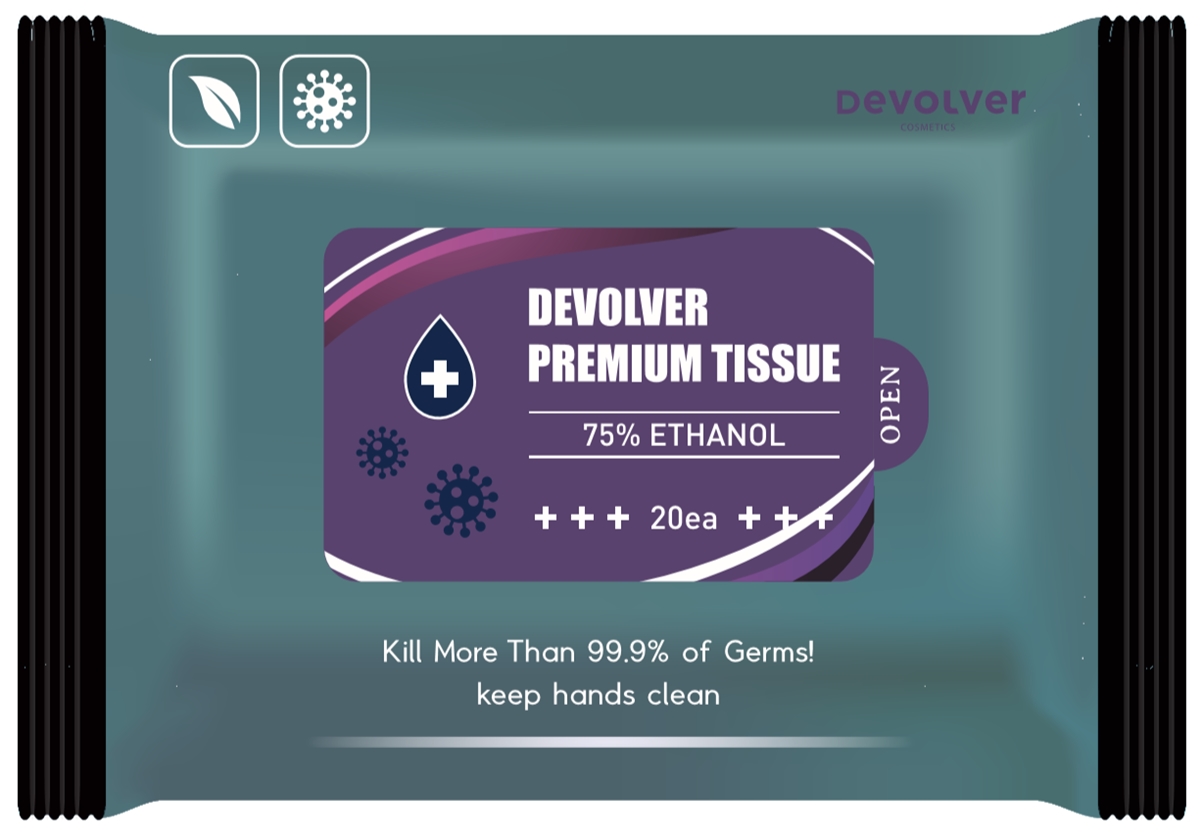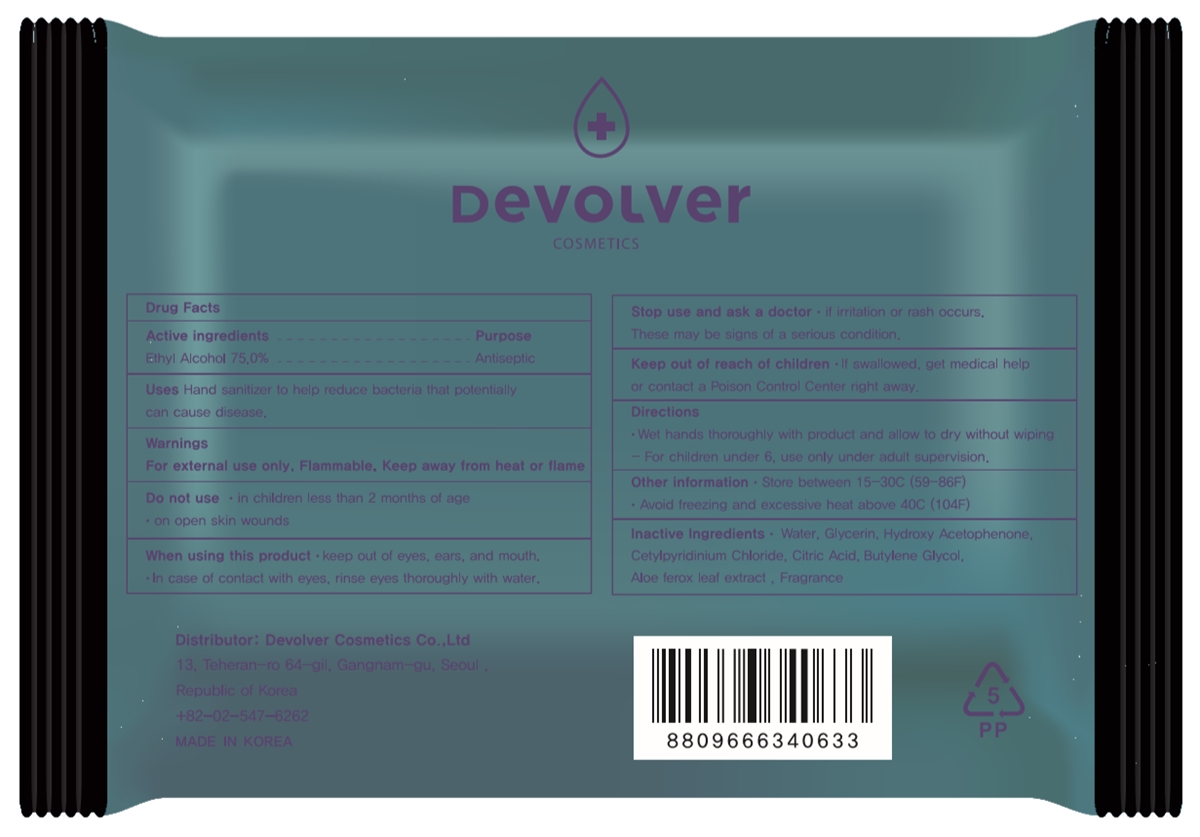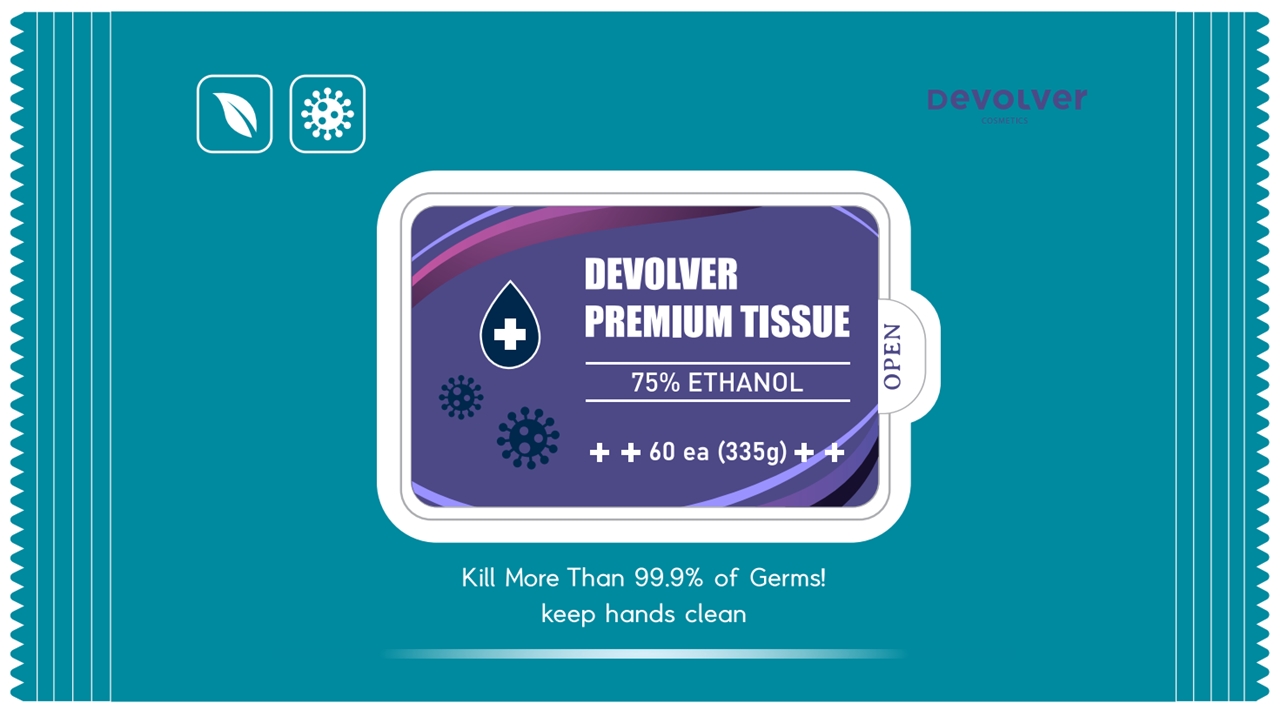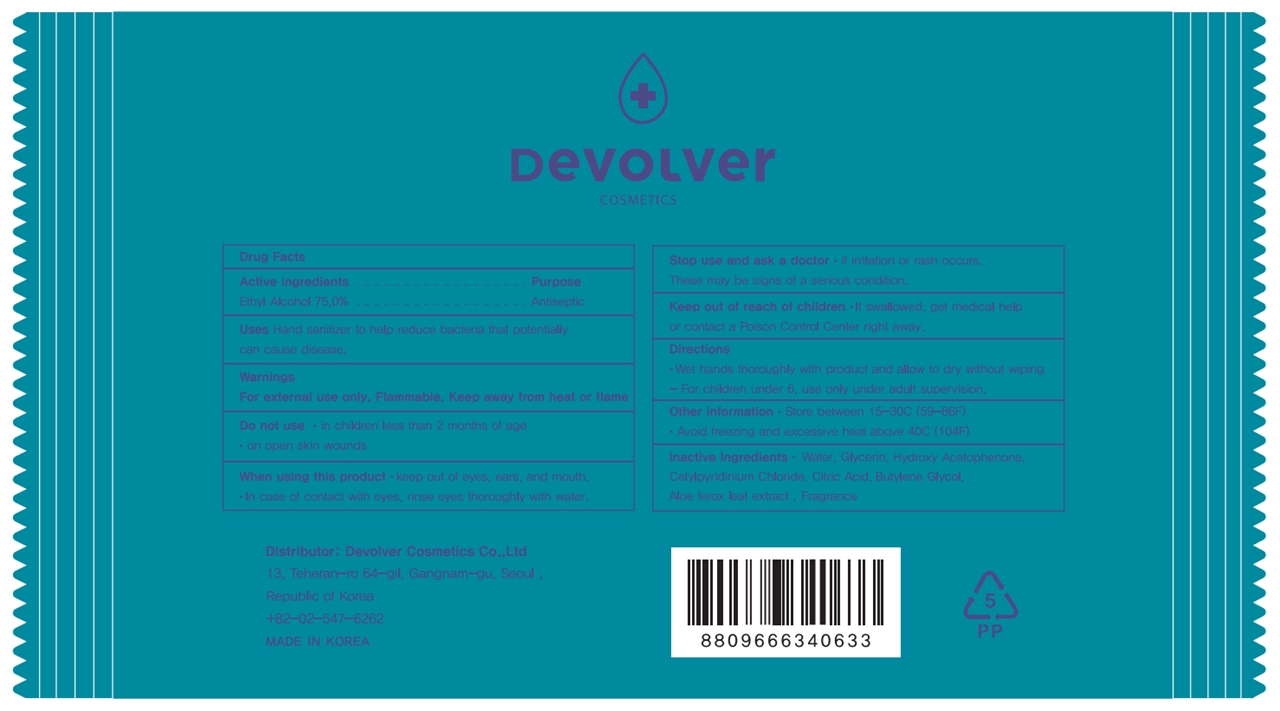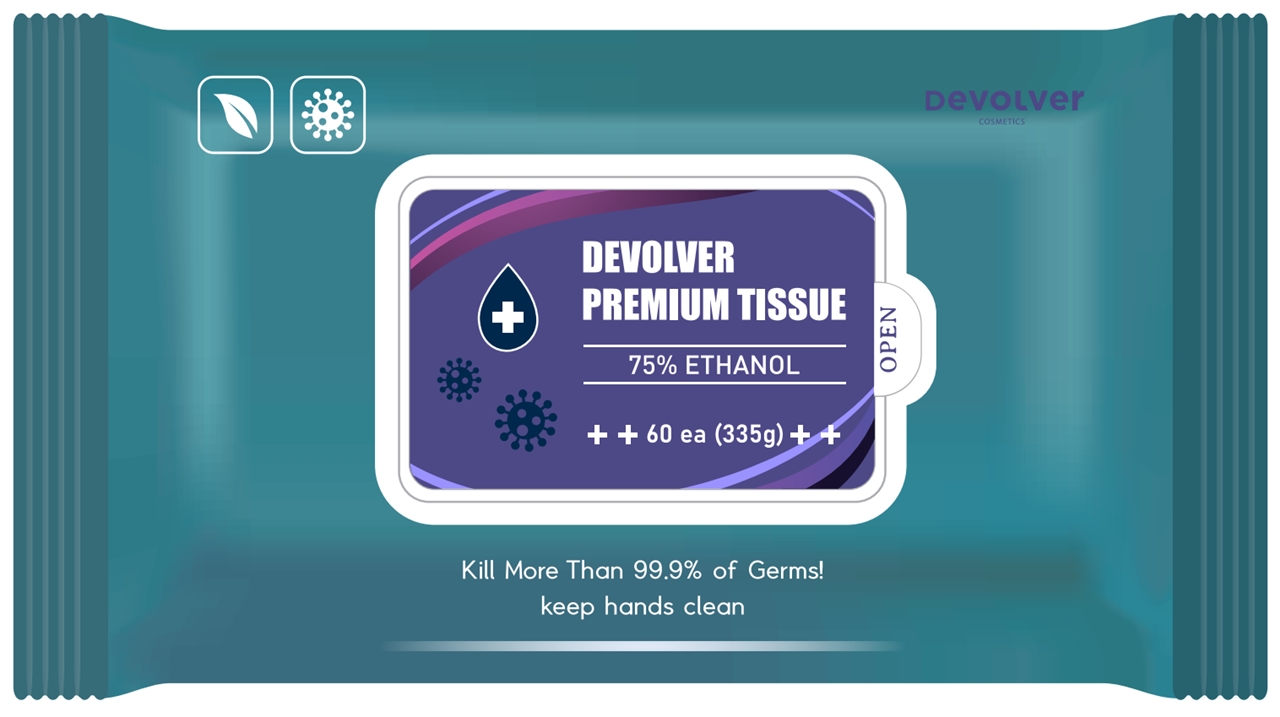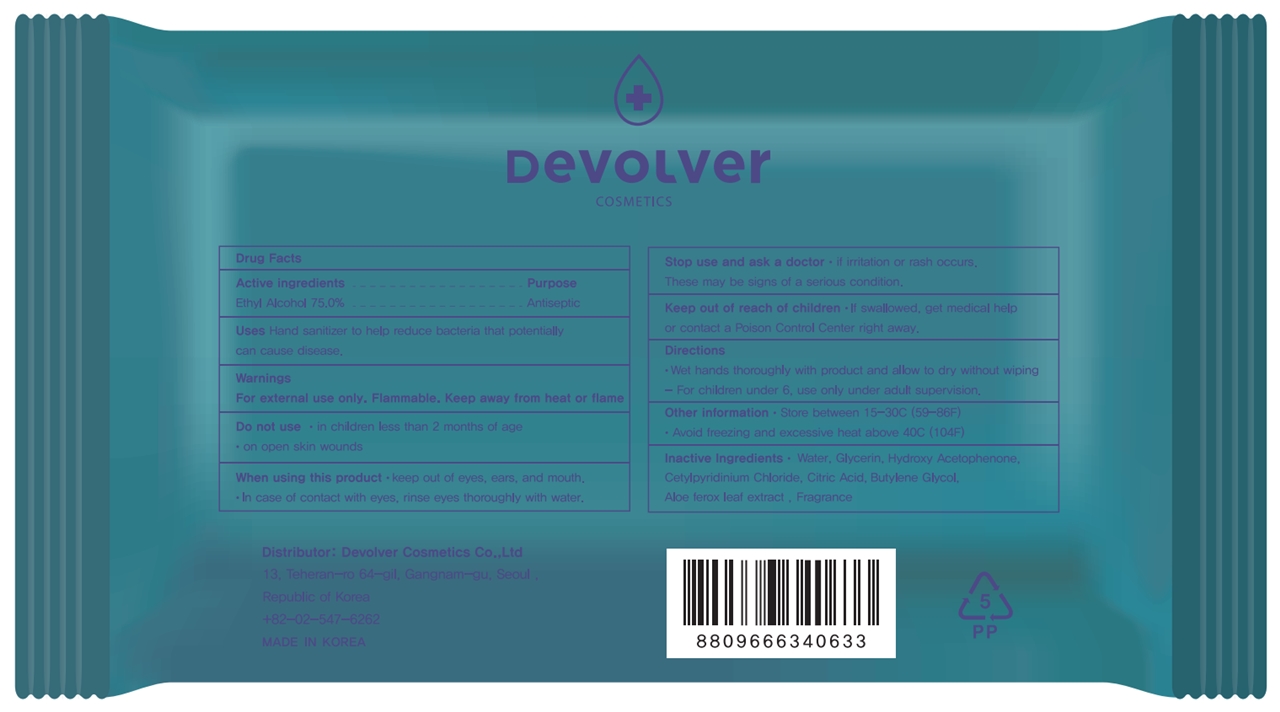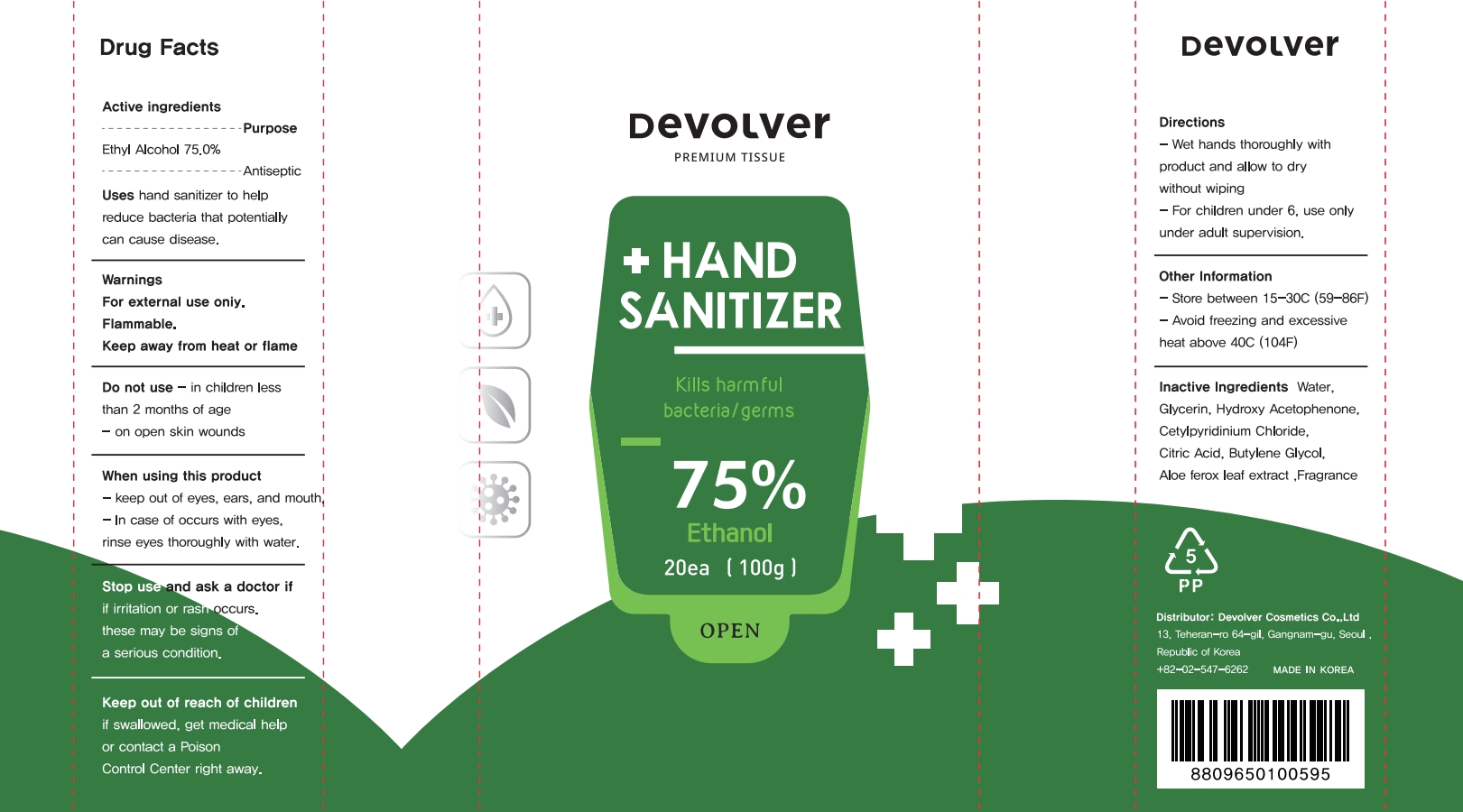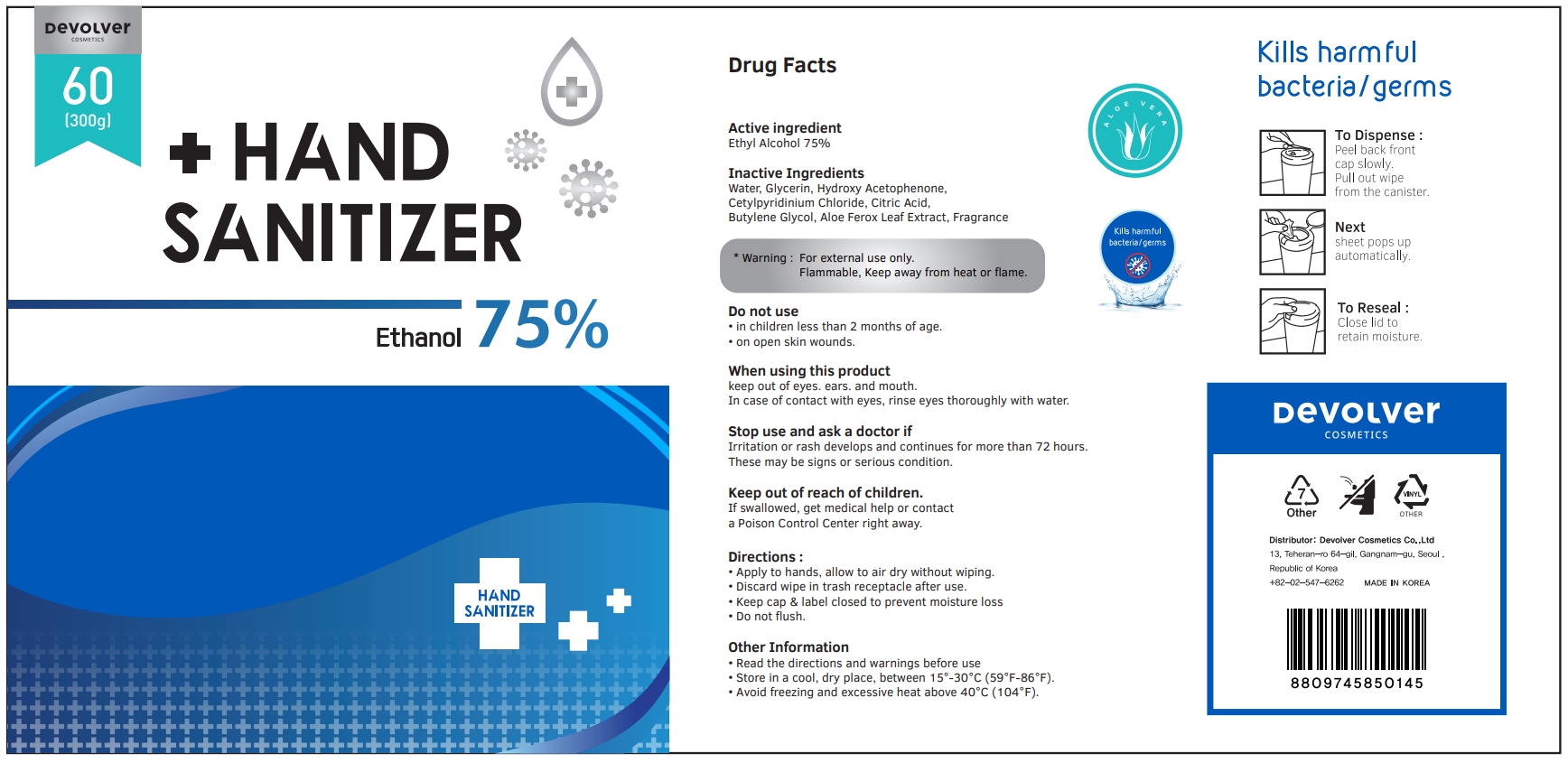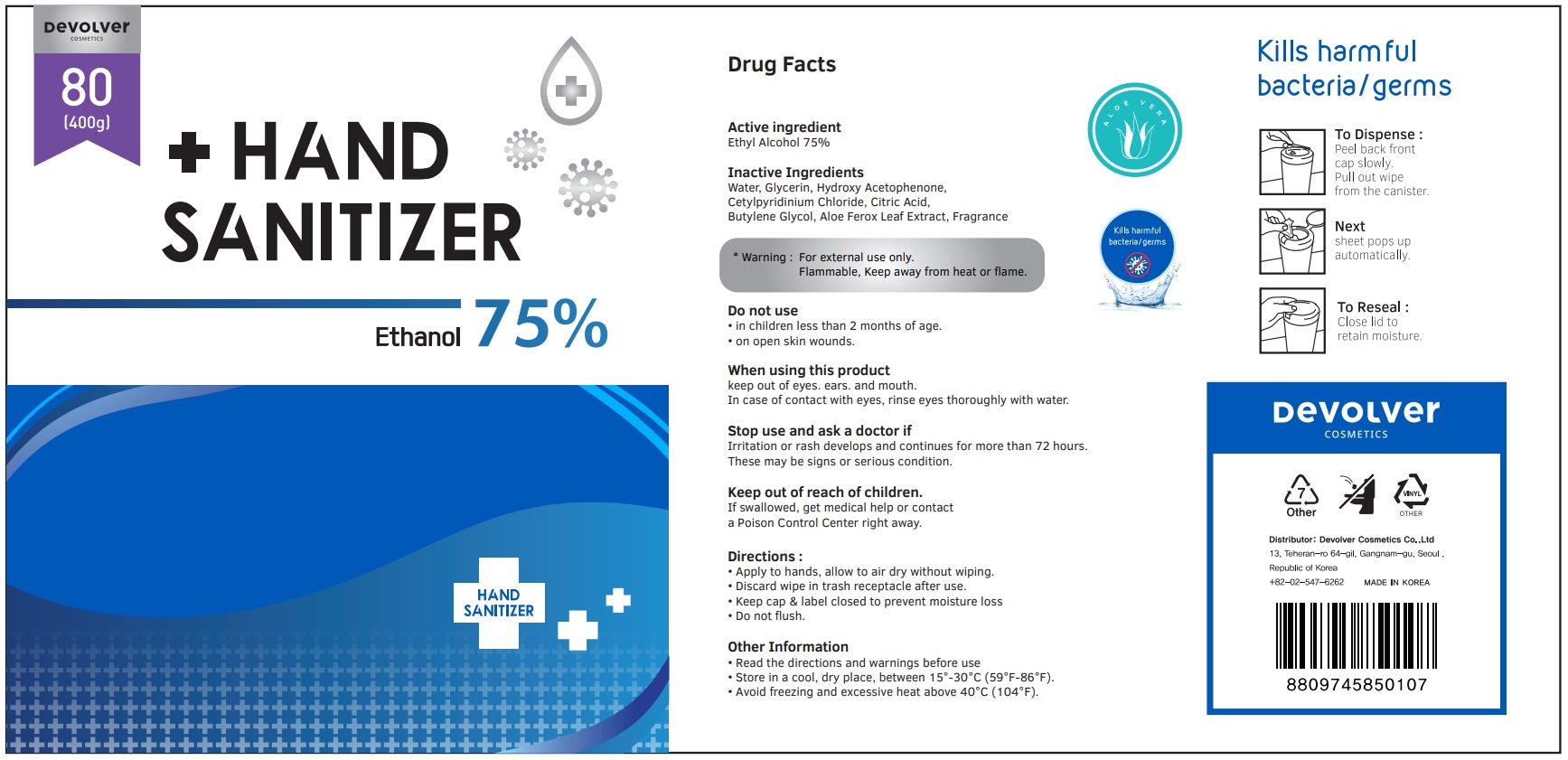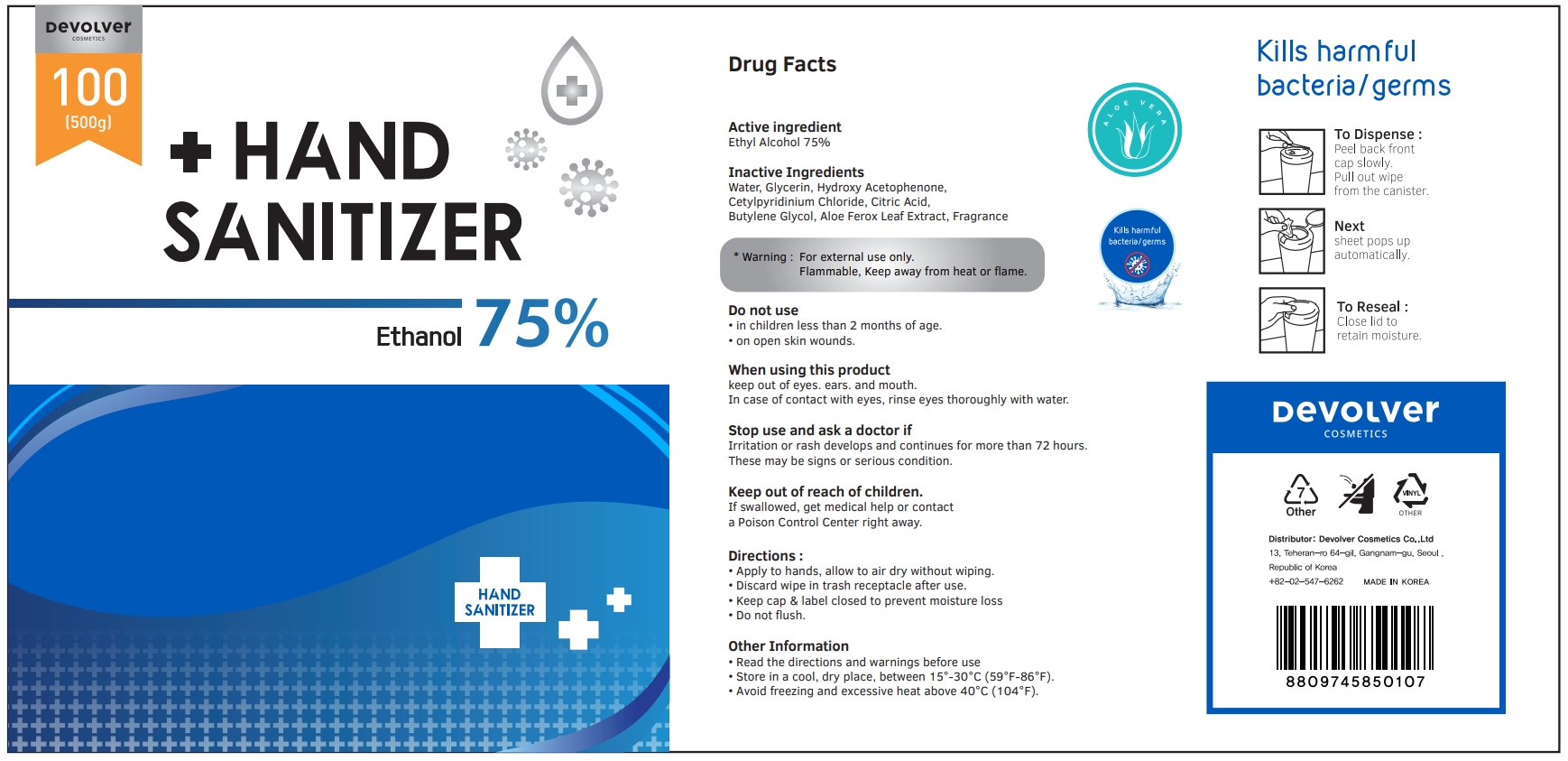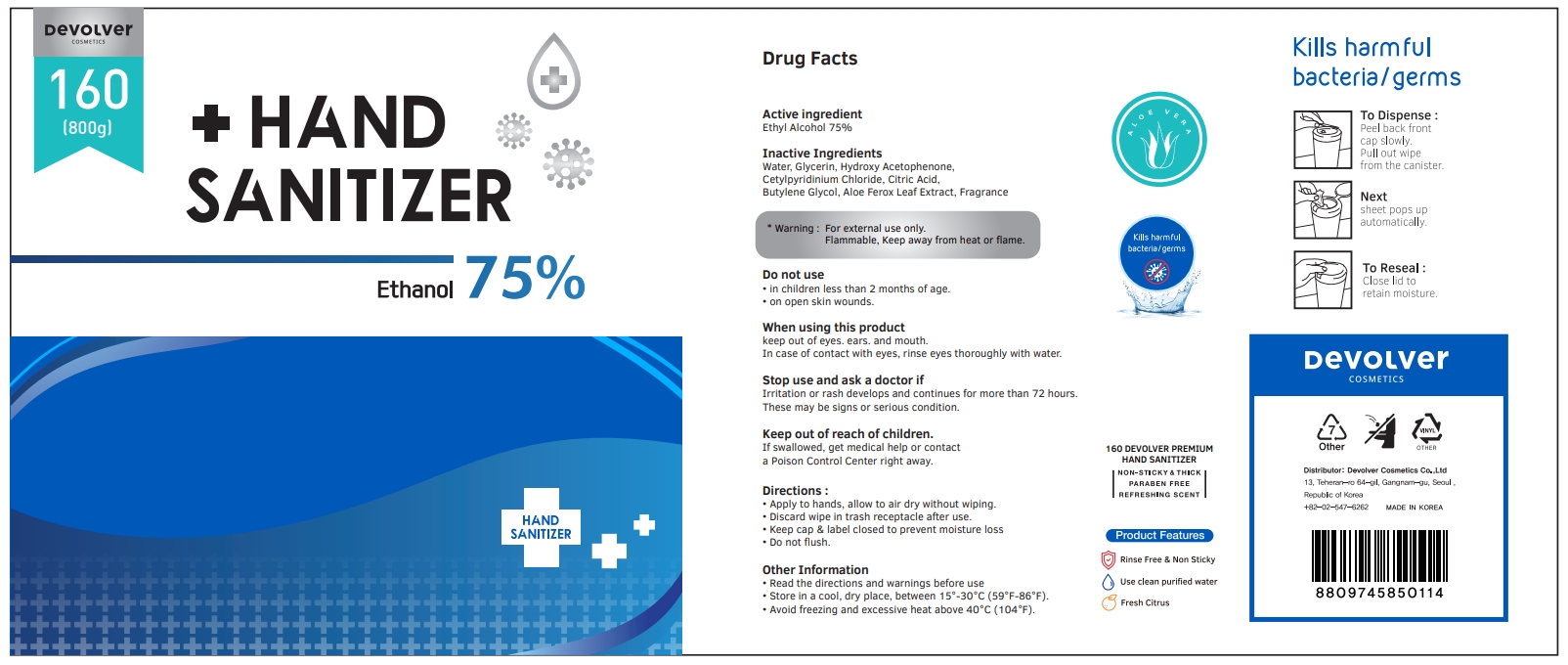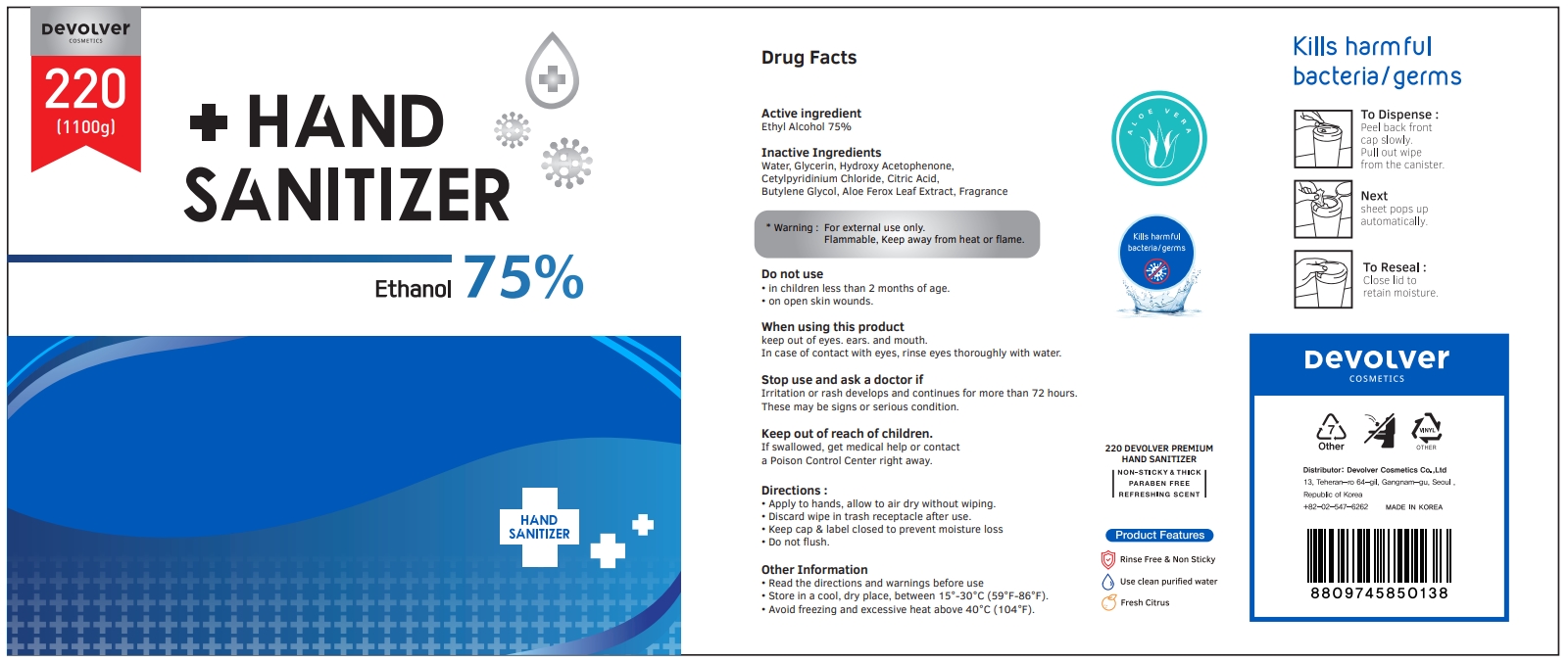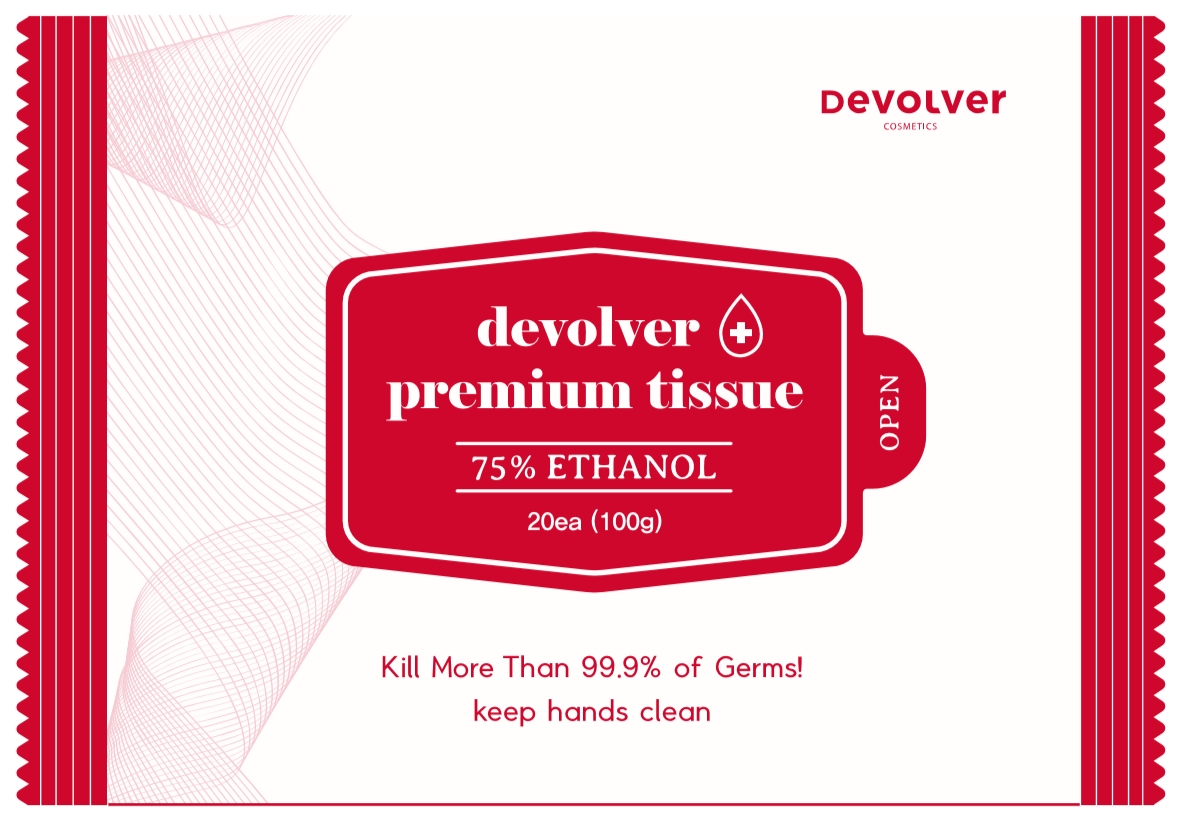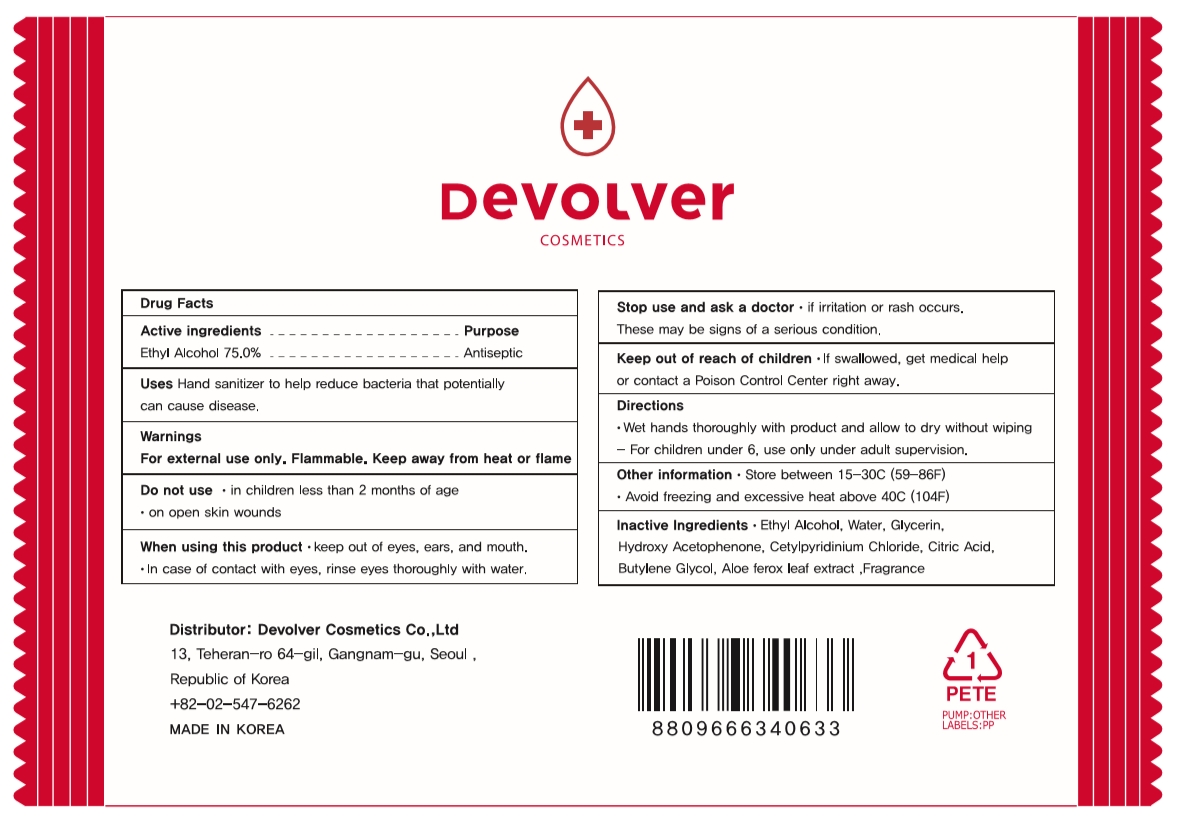 DRUG LABEL: Devolver Premium Tissue
NDC: 75001-204 | Form: LIQUID
Manufacturer: Devolver Cosmetics Co., Ltd
Category: otc | Type: HUMAN OTC DRUG LABEL
Date: 20200730

ACTIVE INGREDIENTS: ALCOHOL 75 g/100 g
INACTIVE INGREDIENTS: ALOE FEROX LEAF; CETYLPYRIDINIUM CHLORIDE; LIME (CALCIUM OXIDE); WATER; GLYCERIN; CITRIC ACID MONOHYDRATE; BUTYLENE GLYCOL; HYDROXYACETOPHENONE

75001-204

Active ingredient

Ethyl Alcohol 75%

Purpose

Antiseptic

Uses

Hand sanitizer to help reduce bacteria that potentially can cause disease.

Warnings

For external use only. Flammable. Keep away from heat or flame

Do not use

in children less than 2 months of age

on open skin wounds

When using this product

keep out of eyes, ears, and mouth.

In case of contact with eyes, rinse eyes thoroughly with water.

Stop use and ask a doctor

if irritation or rash occurs.

These may be signs of a serious condition.

Keep out of reach of children

If swallowed, get medical help or contact a Poison Control Center right away.

Directions

Wet hands thoroughly with product and allow to dry without wiping

For children under 6, use only under adult supervision

Other information

Store between 15-30C (59-86F)

Avoid freezing and excessive heat above 40C (104F)

Inactive Ingredients

Water, Glycerin, Hydroxy Acetophenone, Cetylpyridinium Chloride, Citric Acid, Butylene Glycol, Aloe ferox leaf extract, Fragrance (Lime)